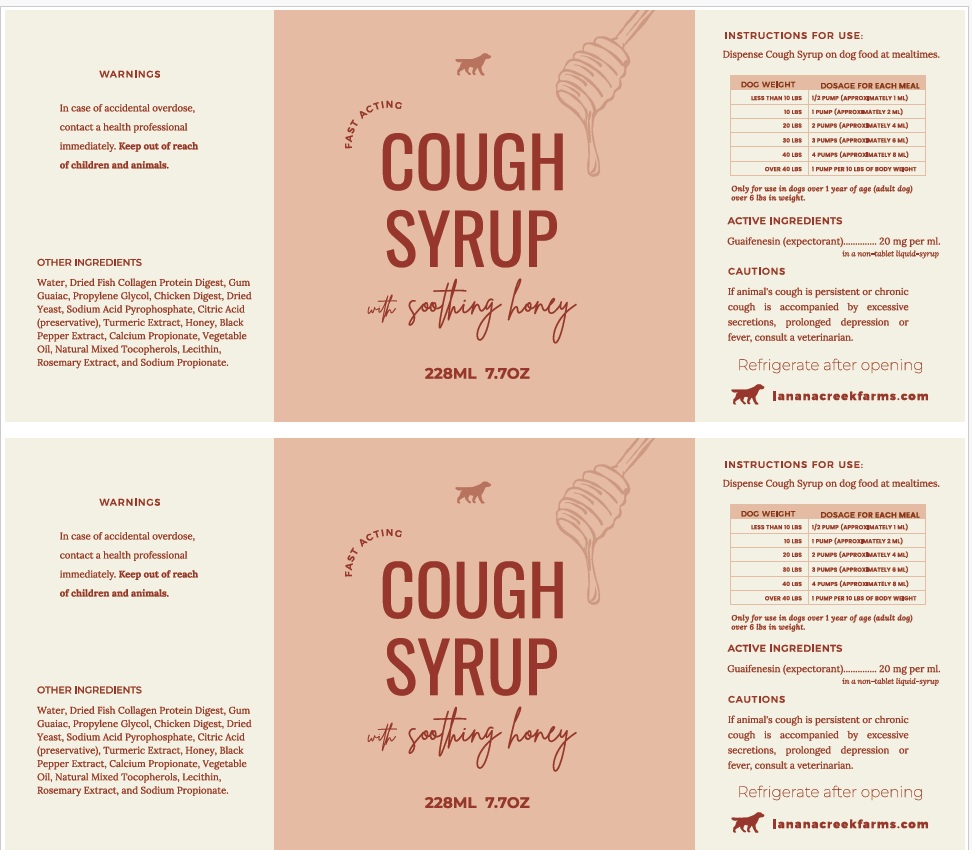 DRUG LABEL: Lanana Creek Farms Cough Syrup
NDC: 57932-008 | Form: LIQUID
Manufacturer: Animal Science Products, Inc.
Category: animal | Type: OTC ANIMAL DRUG LABEL
Date: 20250414

ACTIVE INGREDIENTS: GUAIFENESIN 20 mg/1 mL
INACTIVE INGREDIENTS: WATER; MARINE COLLAGEN, SOLUBLE; GUAIAC; PROPYLENE GLYCOL; CHICKEN; SACCHAROMYCES CEREVISIAE; SODIUM ACID PYROPHOSPHATE; CITRIC ACID MONOHYDRATE; TURMERIC; HONEY; BLACK PEPPER; CALCIUM PROPIONATE; CORN OIL; TOCOPHEROL; SOYBEAN LECITHIN; ROSEMARY; SODIUM PROPIONATE

Active Ingredient

Guaifenesin (expectorant) ...............................20mg per ml. in a non-tablet liquid-syrup

Purpose

Expectorant - helps break-up the mucous in the dog's chest so they can expel it and breathe easier.

Uses

Dogs Greater 1 Year of Age and over 61bs

Warnings

In case of accidental overdose, contact a health professional immediately. Keep away from children and pets.

Cautions

If animal's cough is persistent or chronic cough is accompanied by excessive secretions, prolonged depression or fever, consult a veterinarian.

Directions

Dispense Cough Syrup on Foods at Mealtimes. Refer to dosage chart based on dog's weight on label.
Only for use in dogs over one year in age (adult dog), over 6 pounds in weight.

DOG WEIGHT DOSAGE FOR EACH MEAL

LESS THAN 10 LBS | 1/2 PUMP (APPROXIMATELY 1ML)
10 LBS | 1 PUMP (APPROXIMATELY 2 ML)
20 LBS | 2 PUMP (APPROXIMATELY 4 ML)
30 LBS | 3 PUMP (APPROXIMATELY 6 ML)
40 LBS | 4 PUMP (APPROXIMATELY 8 ML)
Over 40 LBS | 1 PUMP PER 10 LBS OF BODY WEIGHT

Inactive Ingredients

Water, Dried fish collagen protein digest, gum guaiac, propylene glycol, chicken digest, dried yeast, sodium acid pyrophosphate, citric acid, turmeric extract, honey, black pepper extract, calcium propionate, vegetable oil, natural mixed tocopherols, lecithin, rosemary extract, and sodium propionate.